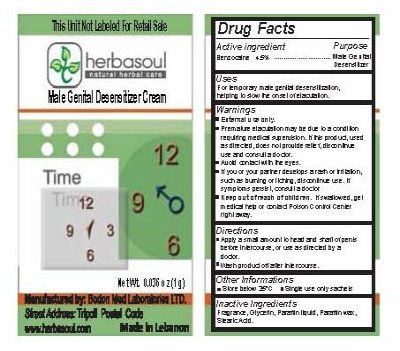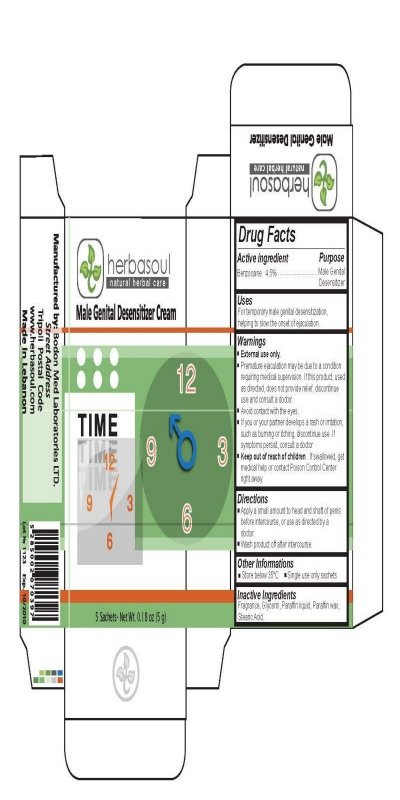 DRUG LABEL: Herbasoul Male Genital Desensitizer Cream
NDC: 50664-100 | Form: CREAM
Manufacturer: Bodon Med Laboratories Ltd.
Category: otc | Type: HUMAN OTC DRUG LABEL
Date: 20100223

ACTIVE INGREDIENTS: BENZOCAINE 4.5 g/100 g
INACTIVE INGREDIENTS: GLYCERIN; MINERAL OIL; STEARIC ACID

Herbasoul Natural Herbal Care Male Genital Desensitizer Cream

Active Ingredient Purpose

Benzocaine 4.5 percent .......................................................................Male Genital

Desensitizer

Uses

For temporary male genital desensitization, helping to slow the onset of ejaculation.

Warnings

External use only.

Premature ejaculation may be due to a condition requiring medical supervision.

If this product, used as directed, does not provide relief, discontinue use. If symptoms persist,
consult a doctor.

Keep out of reach of children.

If swallowed, get medical help or contact Poison Control Center right away.

Directions

Apply a small amount to head and shaft of penis before intercourse,

or use as directed by a doctor.

Wash product off after intercourse.

STORAGE AND HANDLING

Other Informations
Store below 35 celius
Single use only sachets

Inactive Ingredients

Fragrance, Glycerin, Paraffin Liquid, Paraffin wax, Stearic Acid.

DESCRIPTION

Manufactured By: Bodon Med Laboratories LTD.

Street Address

Tripoli Postal Code

www.herbasoul.com

Made in Lebanon

PACKAGE LABEL

This unit not labeled for retail sale

Herbasoul

Natural Herbal Care

Male Genital Desensitizer Cream

Net Wt. 0.036 oz (1 g)